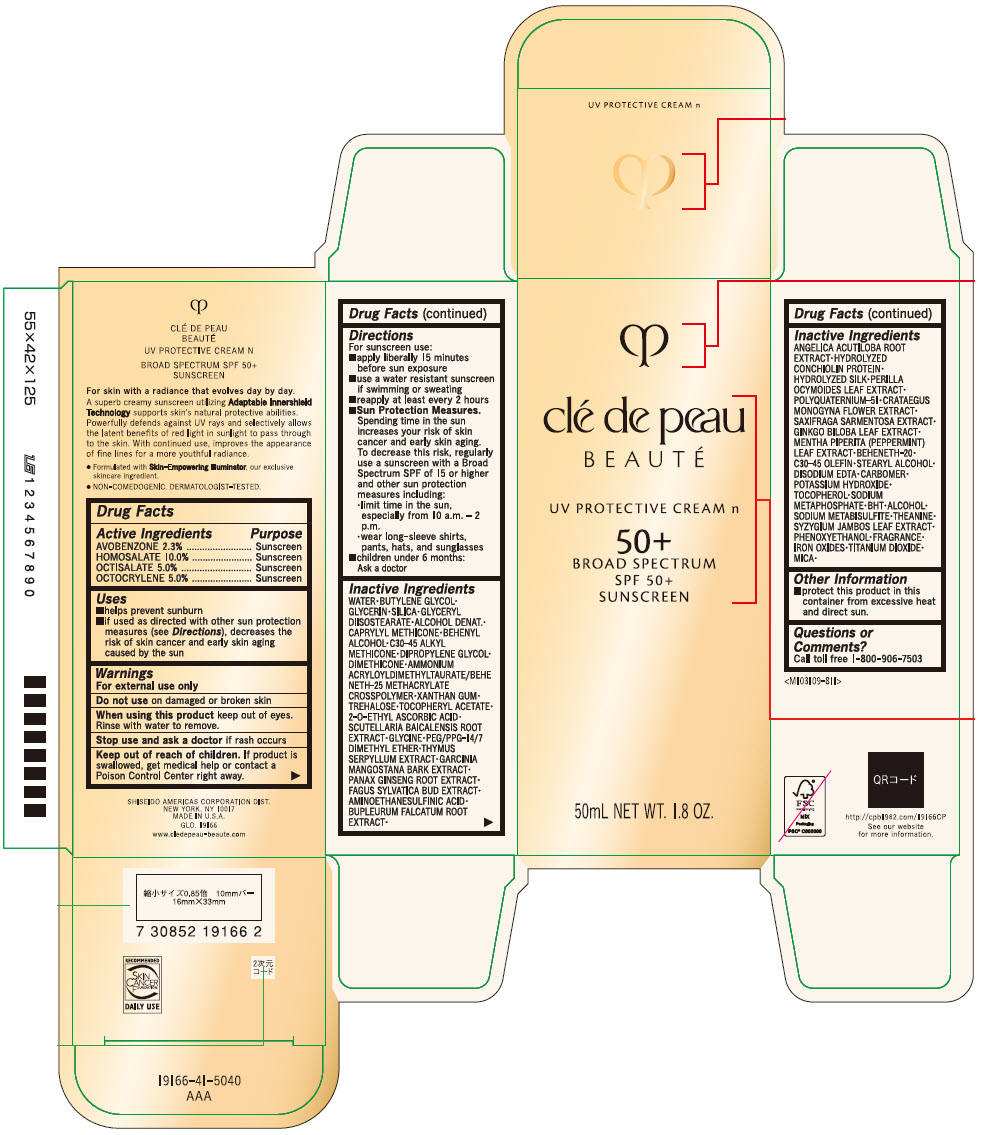 DRUG LABEL: cle de peau BEAUTE UV PROTECTIVE N
NDC: 58411-855 | Form: CREAM
Manufacturer: SHISEIDO AMERICAS CORPORATION
Category: otc | Type: HUMAN OTC DRUG LABEL
Date: 20230130

ACTIVE INGREDIENTS: AVOBENZONE 1.2167 g/50 mL; HOMOSALATE 5.29 g/50 mL; OCTISALATE 2.645 g/50 mL; OCTOCRYLENE 2.645 g/50 mL
INACTIVE INGREDIENTS: WATER; BUTYLENE GLYCOL; GLYCERIN; SILICON DIOXIDE; GLYCERYL DIISOSTEARATE; ALCOHOL; CAPRYLYL TRISILOXANE; DOCOSANOL; C30-45 ALKYL METHICONE; DIPROPYLENE GLYCOL; DIMETHICONE; AMMONIUM ACRYLOYLDIMETHYLTAURATE/BEHENETH-25 METHACRYLATE CROSSPOLYMER (52000 MPA.S); XANTHAN GUM; TREHALOSE; .ALPHA.-TOCOPHEROL ACETATE; 2-O-ETHYL ASCORBIC ACID; SCUTELLARIA BAICALENSIS ROOT; GLYCINE; PEG/PPG-14/7 DIMETHYL ETHER; THYMUS SERPYLLUM WHOLE; GARCINIA MANGOSTANA BARK; ASIAN GINSENG; FAGUS SYLVATICA FLOWER BUD; HYPOTAURINE; BUPLEURUM FALCATUM ROOT; ANGELICA ACUTILOBA ROOT; PERILLA FRUTESCENS LEAF; POLYQUATERNIUM-51 (2-METHACRYLOYLOXYETHYL PHOSPHORYLCHOLINE/N-BUTYL METHACRYLATE; 4:1); CRATAEGUS MONOGYNA FLOWER; SAXIFRAGA STOLONIFERA LEAF; GINKGO; MENTHA PIPERITA LEAF; BEHENETH-20; C30-45 OLEFIN; STEARYL ALCOHOL; EDETATE DISODIUM; CARBOMER HOMOPOLYMER TYPE A (ALLYL PENTAERYTHRITOL CROSSLINKED); POTASSIUM HYDROXIDE; TOCOPHEROL; SODIUM METAPHOSPHATE; BUTYLATED HYDROXYTOLUENE; SODIUM METABISULFITE; THEANINE; SYZYGIUM JAMBOS LEAF; PHENOXYETHANOL; FERRIC OXIDE RED; TITANIUM DIOXIDE; MICA

clé de peau BEAUTÉ UV PROTECTIVE CREAM N

Drug Facts

ACTIVE INGREDIENT

Active ingredients | Purpose
AVOBENZONE 2.3% | Sunscreen
HOMOSALATE 10.0% | Sunscreen
OCTISALATE 5.0% | Sunscreen
OCTOCRYLENE 5.0% | Sunscreen

Uses

- helps prevent sunburn
- if used as directed with other sun protection measures (see Directions), decreases the risk of skin cancer and early skin aging caused by the sun

Warnings

For external use only

Do not use on damaged or broken skin

When using this product keep out of eyes. Rinse with water to remove.

Stop use and ask a doctor if rash occurs

Keep out of reach of children. If product is swallowed, get medical help or contact a Poison Control Center right away.

Directions

For sunscreen use:

- apply liberally 15 minutes before sun exposure
- use a water resistant sunscreen if swimming or sweating
- reapply at least every 2 hours
- Sun Protection Measures. Spending time in the sun increases your risk of skin cancer and early skin aging. To decrease this risk, regularly use a sunscreen with a Broad Spectrum SPF of 15 or higher and other sun protection measures including:
  - limit time in the sun, especially from 10 a.m. – 2 p.m.
  - wear long-sleeve shirts, pants, hats, and sunglasses
- children under 6 months: Ask a doctor

Inactive ingredients

WATER▪BUTYLENE GLYCOL▪GLYCERIN▪SILICA▪GLYCERYL DIISOSTEARATE▪ALCOHOL DENAT.▪CAPRYLYL METHICONE▪BEHENYL ALCOHOL▪C30-45 ALKYL METHICONE▪DIPROPYLENE GLYCOL▪DIMETHICONE▪AMMONIUM ACRYLOYLDIMETHYLTAURATE/BEHENETH-25 METHACRYLATE CROSSPOLYMER▪XANTHAN GUM▪TREHALOSE▪TOCOPHERYL ACETATE▪2-O-ETHYL ASCORBIC ACID▪SCUTELLARIA BAICALENSIS ROOT EXTRACT▪GLYCINE▪PEG/PPG-14/7 DIMETHYL ETHER▪THYMUS SERPYLLUM EXTRACT▪GARCINIA MANGOSTANA BARK EXTRACT▪PANAX GINSENG ROOT EXTRACT▪FAGUS SYLVATICA BUD EXTRACT▪AMINOETHANESULFINIC ACID▪BUPLEURUM FALCATUM ROOT EXTRACT▪ANGELICA ACUTILOBA ROOT EXTRACT▪HYDROLYZED CONCHIOLIN PROTEIN▪HYDROLYZED SILK▪PERILLA OCYMOIDES LEAF EXTRACT▪POLYQUATERNIUM-51▪CRATAEGUS MONOGYNA FLOWER EXTRACT▪SAXIFRAGA SARMENTOSA EXTRACT▪GINKGO BILOBA LEAF EXTRACT▪MENTHA PIPERITA (PEPPERMINT) LEAF EXTRACT▪BEHENETH-20▪C30-45 OLEFIN▪STEARYL ALCOHOL▪DISODIUM EDTA▪CARBOMER▪POTASSIUM HYDROXIDE▪TOCOPHEROL▪SODIUM METAPHOSPHATE▪BHT▪ALCOHOL▪SODIUM METABISULFITE▪THEANINE▪SYZYGIUM JAMBOS LEAF EXTRACT▪PHENOXYETHANOL▪FRAGRANCE▪IRON OXIDES▪TITANIUM DIOXIDE▪MICA▪

Other information

- protect this product in this container from excessive heat and direct sun.

Questions or comments?

Call toll free 1-800-906-7503

PRINCIPAL DISPLAY PANEL - 50 mL Tube Carton

clé de peau
BEAUTÉ

UV PROTECTIVE CREAM n

50+

BROAD SPECTRUM
SPF 50+
SUNSCREEN

50mL NET WT. 1.8 OZ.